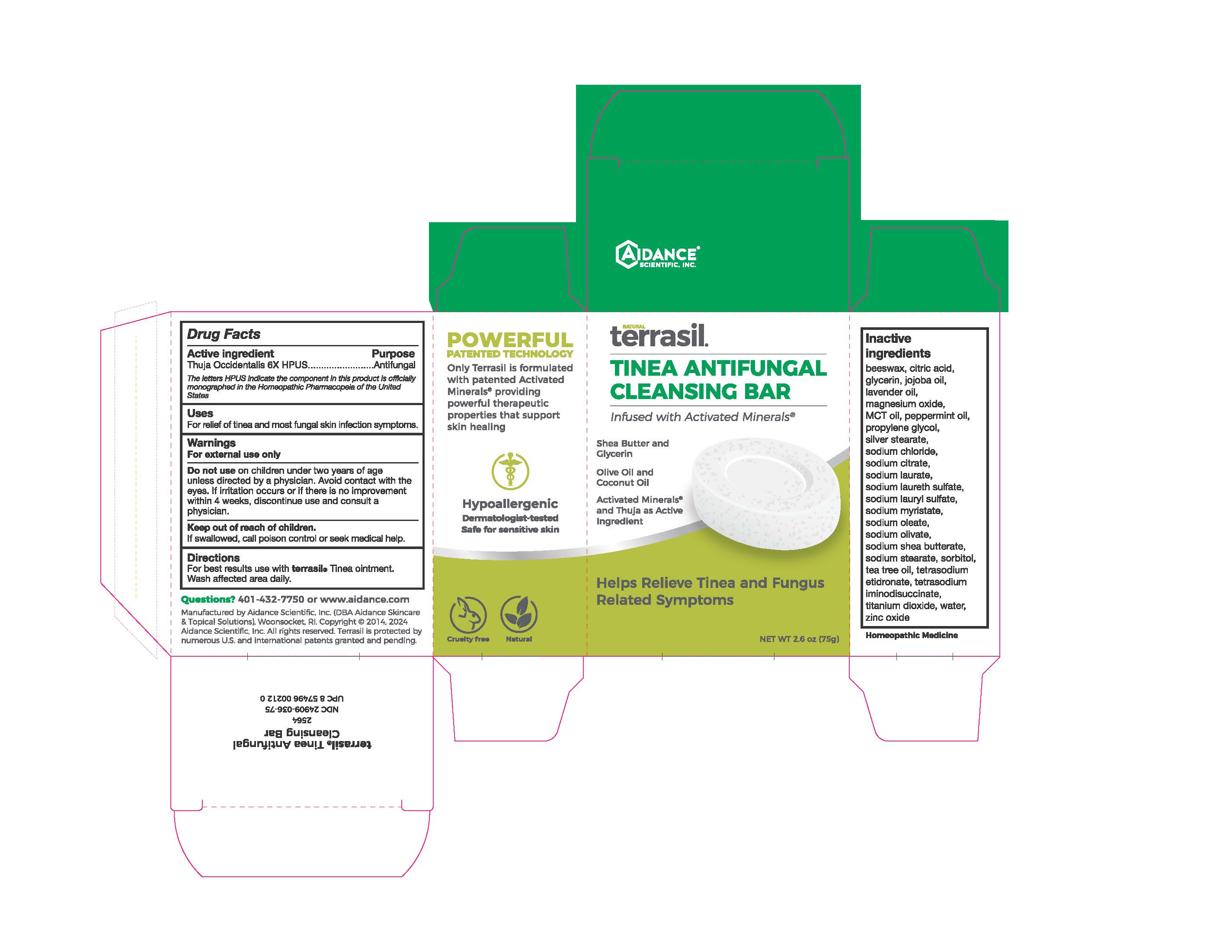 DRUG LABEL: Terrasil Tinea Antifungal Cleansing Bar
NDC: 24909-036 | Form: SOAP
Manufacturer: Aidance Scientific, Inc, DBA Aidance Skincare & Topical Solutions
Category: homeopathic | Type: HUMAN OTC DRUG LABEL
Date: 20240524

ACTIVE INGREDIENTS: THUJA OCCIDENTALIS WHOLE 6 [hp_X]/1 g
INACTIVE INGREDIENTS: PROPYLENE GLYCOL; SHEA BUTTER; YELLOW WAX; MEDIUM-CHAIN TRIGLYCERIDES; JOJOBA OIL; GLYCERIN; LAVENDER OIL; MAGNESIUM OXIDE; PEPPERMINT OIL; SODIUM CHLORIDE; SODIUM CITRATE; SODIUM LAURATE; SODIUM LAURETH SULFATE; SODIUM LAURYL SULFATE; SODIUM MYRISTATE; SODIUM OLEATE; SODIUM OLIVATE; SODIUM STEARATE; SORBITOL; TEA TREE OIL; ETIDRONATE TETRASODIUM; TITANIUM DIOXIDE; WATER; ZINC OXIDE; SILVER STEARATE; CITRIC ACID MONOHYDRATE; TETRASODIUM IMINODISUCCINATE

24909-036 terrasil Tinea Antifungal Cleansing Bar

Active Ingredient

Thuja Occidentalis 6X HPUS

Purpose

Antifungal

Uses

For relief of tinea and most fungal skin infection symptoms.

Warnings

For external use only.

Do not use on children under two years of age unless directed by a physician. Avoid contact with the eyes. If irritation occurs or if there is no improvement within 4 weeks, discontinue use and consult a physician.

Keep out of reach of children. If swallowed, call poison control or seek medical help.

Directions

For best results use with terrasil® Tinea Treatment ointment products. Wash affected area daily.

Inactive Ingredients

beeswax, citric acid, glycerin, jojoba oil, lavender oil, magnesium oxide, peppermint oil, propylene glycol, silver stearate, sodium chloride, sodium citrate, sodium laurate, sodium laureth sulfate, sodium lauryl sulfate, sodium myristate, sodium oleate, sodium olivate, sodium shea butterate, sodium stearate, sorbitol, tea tree oil, tetrasodium etidronate, tetrasodium iminodisuccinate, titanium dioxide, water, zinc oxide